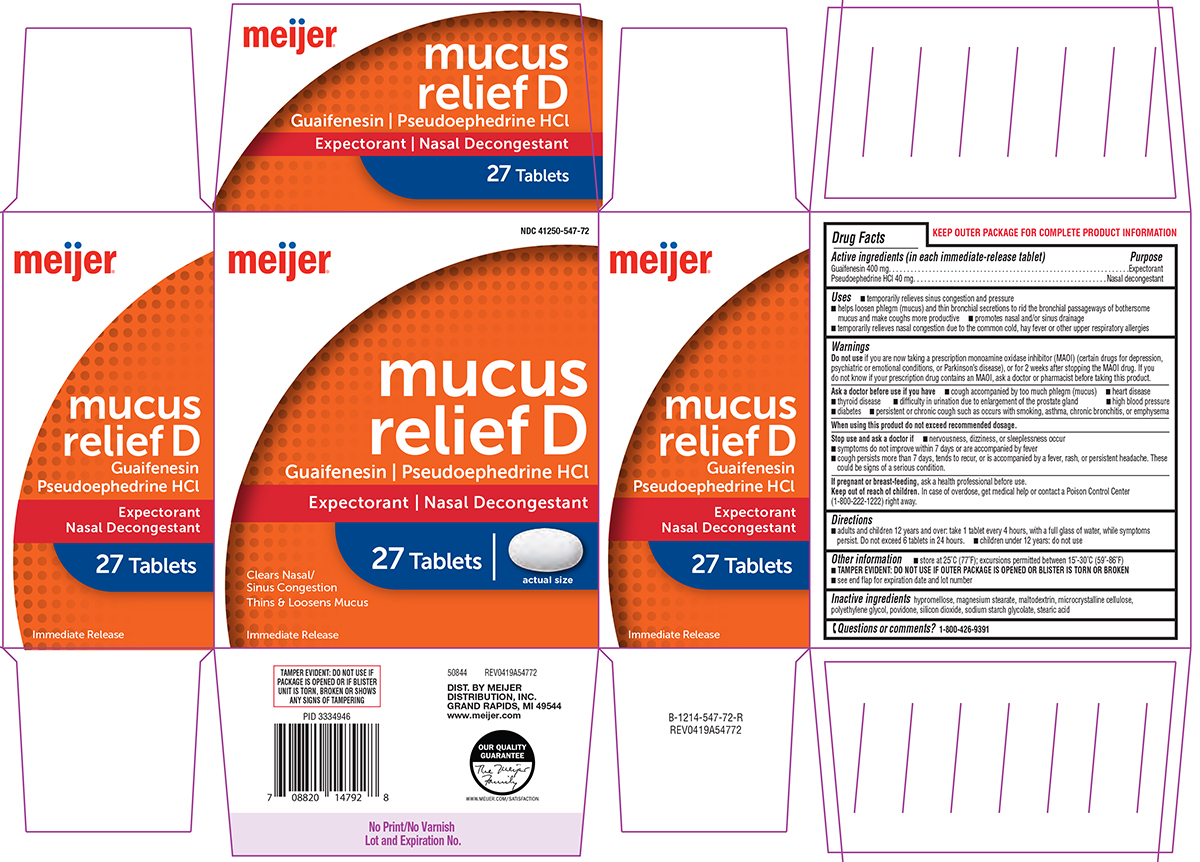 DRUG LABEL: Mucus Relief D
NDC: 41250-547 | Form: TABLET, FILM COATED
Manufacturer: Meijer Distribution Inc
Category: otc | Type: HUMAN OTC DRUG LABEL
Date: 20250826

ACTIVE INGREDIENTS: GUAIFENESIN 400 mg/1 1; PSEUDOEPHEDRINE HYDROCHLORIDE 40 mg/1 1
INACTIVE INGREDIENTS: HYPROMELLOSE, UNSPECIFIED; MAGNESIUM STEARATE; MALTODEXTRIN; MICROCRYSTALLINE CELLULOSE; POLYETHYLENE GLYCOL, UNSPECIFIED; POVIDONE, UNSPECIFIED; SILICON DIOXIDE; SODIUM STARCH GLYCOLATE TYPE A POTATO; STEARIC ACID

Meijer 44-547

Active ingredients (in each immediate-release tablet)

Guaifenesin 400 mg
Pseudoephedrine HCl 40 mg

Purpose

Expectorant
Nasal decongestant

Uses

- temporarily relieves sinus congestion and pressure
- helps loosen phlegm (mucus) and thin bronchial secretions to rid the bronchial passageways of bothersome mucus and make coughs more productive
- promotes nasal and/or sinus drainage
- temporarily relieves nasal congestion due to the common cold, hay fever or other upper respiratory allergies

Warnings

Do not use

if you are now taking a prescription monoamine oxidase inhibitor (MAOI) (certain drugs for depression, psychiatric or emotional conditions, or Parkinson's disease), or for 2 weeks after stopping the MAOI drug. If you do not know if your prescription drug contains an MAOI, ask a doctor or pharmacist before taking this product.

Ask a doctor before use if you have

- cough accompanied by too much phlegm (mucus)
- heart disease
- thyroid disease
- difficulty in urination due to enlargement of the prostate gland
- high blood pressure
- diabetes
- persistent or chronic cough such as occurs with smoking, asthma, chronic bronchitis, or emphysema

When using this product

do not exceed recommended dosage.

Stop use and ask a doctor if

- nervousness, dizziness, or sleeplessness occur
- symptoms do not improve within 7 days or are accompanied by fever
- cough persists more than 7 days, tends to recur, or is accompanied by a fever, rash, or persistent headache. These could be signs of a serious condition.

If pregnant or breast-feeding,

ask a health professional before use.

Keep out of reach of children.

In case of overdose, get medical help or contact a Poison Control Center (1-800-222-1222) right away.

Directions

- adults and children 12 years and over: take 1 tablet every 4 hours, with a full glass of water, while symptoms persist. Do not exceed 6 tablets in 24 hours.
- children under 12 years: do not use

Other information

- store at 25ºC (77ºF); excursions permitted between 15°-30°C (59°-86°F)
- TAMPER EVIDENT: DO NOT USE IF OUTER PACKAGE IS OPENED OR BLISTER IS TORN OR BROKEN
- see end flap for expiration date and lot number

Inactive ingredients

hypromellose, magnesium stearate, maltodextrin, microcrystalline cellulose, polyethylene glycol, povidone, silicon dioxide, sodium starch glycolate, stearic acid

Questions or comments?

1-800-426-9391

Principal Display Panel

NDC 41250-547-72

meijer®

mucus
relief D
Guaifenesin | Pseudoephedrine HCl
Expectorant | Nasal Decongestant

27 Tablets | actual size

Clears Nasal/
Sinus Congestion
Thins & Loosens Mucus

Immediate Release

TAMPER EVIDENT: DO NOT USE IF
PACKAGE IS OPENED OR IF BLISTER
UNIT IS TORN, BROKEN OR SHOWS
ANY SIGNS OF TAMPERING

50844 REV0419A54772

DIST. BY MEIJER
DISTRIBUTION, INC.
GRAND RAPIDS, MI 49544
www.meijer.com

OUR QUALITY
GUARANTEE
The Meijer
Family
WWW.MEIJER.COM/SATISFACTION
Meijer 44-547